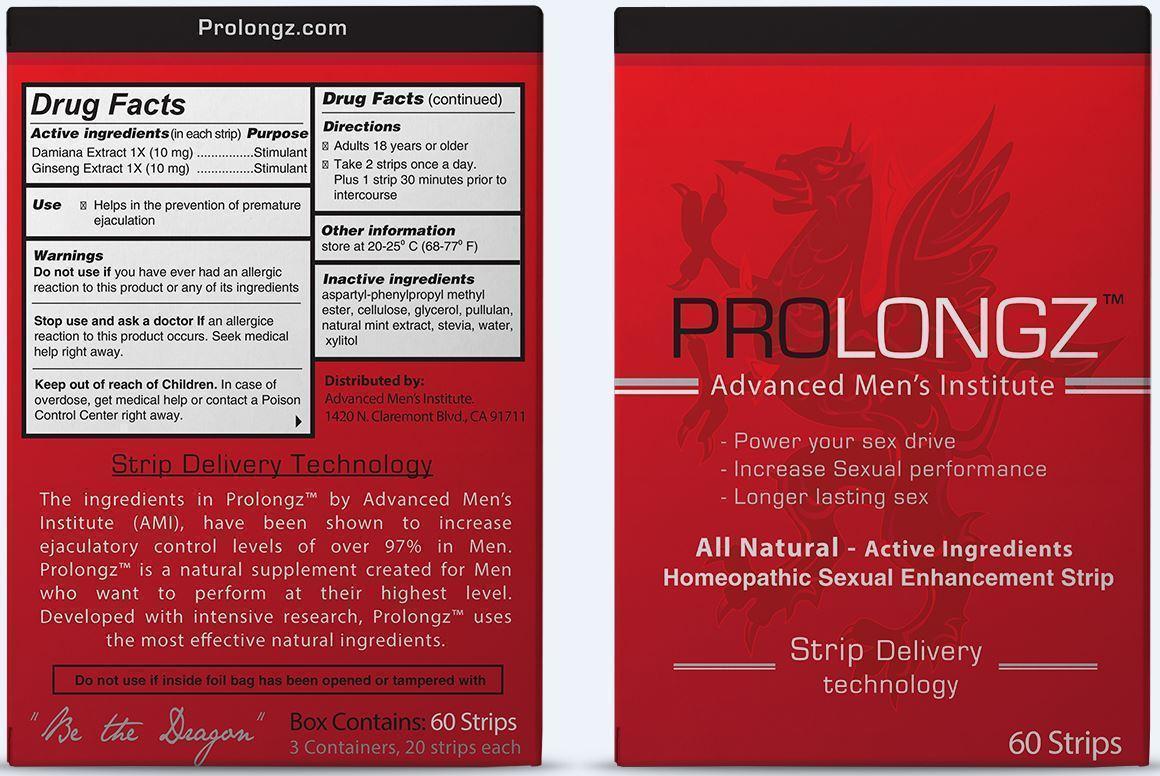 DRUG LABEL: Prolongz
NDC: 69305-000 | Form: STRIP
Manufacturer: Advanced Men's Institute LLC
Category: homeopathic | Type: HUMAN OTC DRUG LABEL
Date: 20180114

ACTIVE INGREDIENTS: TURNERA DIFFUSA LEAF 1 [hp_X]/100 1; ASIAN GINSENG 1 [hp_X]/100 1
INACTIVE INGREDIENTS: POWDERED CELLULOSE; ADVANTAME; GLYCERIN; PULLULAN; MINT; STEVIA REBAUDIUNA LEAF; WATER; XYLITOL

Prolongz

Active Ingredients (in each strip) Purpose

Damiana Extract 1X (10 mg) .................... Stimulant

Ginseng Extract 1X (10 mg) ..................... Stimulant

Use

Helps in the prevention of premature ejaculation

Keep out of reach of children. In case of overdose, get medical help or contact a Poison Control Center right away.

INDICATIONS AND USAGE

PROLONGZ™

Advanced Men's Institute

- Power your sex drive
- Increase Sexual performance
- Longer lasting sex

All Natural - Active Ingredients

Homeopathic Sexual Enhancement Strip

Strip Delivery technology

60 Strips

Strip Delivery Technology

The ingredients in Prolongz™ by Advanced Men's Institute (AMI), have been shown to increase ejaculatory control levels of over 90% in Men. Prolongz™ is a natural supplement created for Men who want to perform at their highest level. Developed with intensive research, Prolongz™ uses the most effective natural ingredients.

" Be the Dragon"

Warnings

Do not use if you have ever had an allergic reaction to this product or any of its ingredients

Stop use and ask a doctor if an allergic reaction to this product occurs.

Directions

- Adults 18 years or older
- Take 2 strips once a day. Plus 1 strip 30 minutes prior to intercourse

Inactive Ingredients

aspartyl-phenylpropyl methyl ester, cellulose, glycerol, pullulan, natural mint extract, stevia, water, xylitol